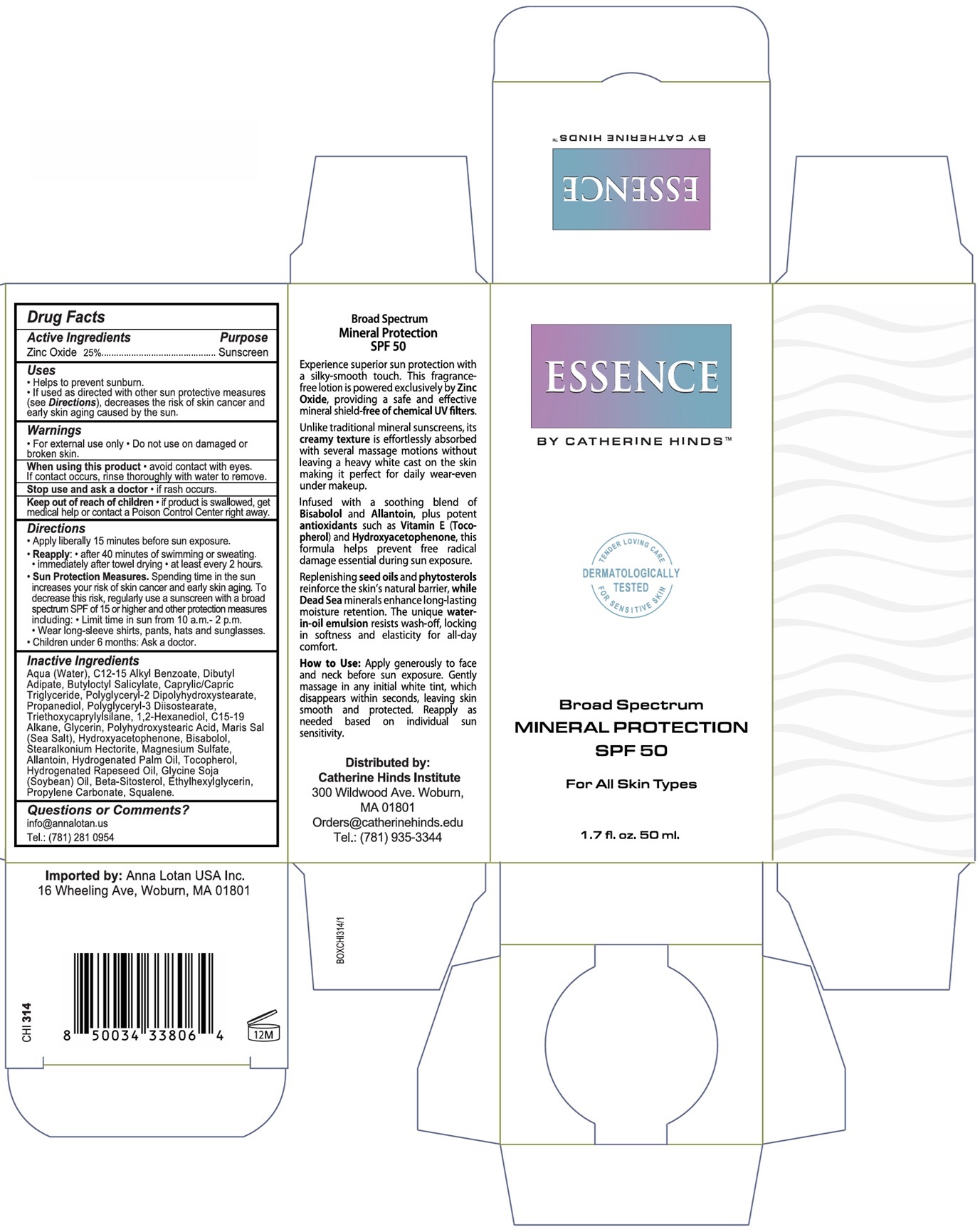 DRUG LABEL: ESSENCE BY CATHERINE HINDS Broad Spectrum MINERAL PROTECTION SPF 50
NDC: 87207-314 | Form: LOTION
Manufacturer: Catherine Hinds Company, Inc.
Category: otc | Type: HUMAN OTC DRUG LABEL
Date: 20251110

ACTIVE INGREDIENTS: ZINC OXIDE 25 g/100 mL
INACTIVE INGREDIENTS: WATER; ALKYL (C12-15) BENZOATE; DIBUTYL ADIPATE; BUTYLOCTYL SALICYLATE; MEDIUM-CHAIN TRIGLYCERIDES; POLYGLYCERYL-2 DIPOLYHYDROXYSTEARATE; PROPANEDIOL; POLYGLYCERYL-3 DIISOSTEARATE; TRIETHOXYCAPRYLYLSILANE; 1,2-HEXANEDIOL; C15-19 ALKANE; GLYCERIN; POLYHYDROXYSTEARIC ACID (2300 MW); SEA SALT; HYDROXYACETOPHENONE; LEVOMENOL; STEARALKONIUM HECTORITE; MAGNESIUM SULFATE, UNSPECIFIED FORM; ALLANTOIN; HYDROGENATED PALM OIL; TOCOPHEROL; HYDROGENATED RAPESEED OIL; SOYBEAN OIL; .BETA.-SITOSTEROL; ETHYLHEXYLGLYCERIN; PROPYLENE CARBONATE; SQUALENE

ESSENCE BY CATHERINE HINDS™ Broad Spectrum MINERAL PROTECTION SPF 50

Active Ingredients

Zinc Oxide 25%

Purpose

Sunscreen

Uses

• Helps to prevent sunburn.
• If used as directed with other sun protective measures (see Directions), decreases the risk of skin cancer and early skin aging caused by the sun.

Warnings

• For external use only • Do not use on damaged or broken skin.

When using this product • avoid contact with eyes. If contact occurs, rinse thoroughly with water to remove.

Stop use and ask a doctor • if rash occurs.

Keep out of reach of children • if product is swallowed, get medical help or contact a Poison Control Center right away.

Directions

• Apply liberally 15 minutes before sun exposure.
• Reapply: • after 40 minutes of swimming or sweating • immediately after towel drying • at least every 2 hours.
• Sun Protection Measures. Spending time in the sun increases your risk of skin cancer and early skin aging. To decrease this risk, regularly use a sunscreen with a broad spectrum SPF of 15 or higher and other protection measures including: • Limit time in sun from 10 a.m.- 2 p.m. • Wear long-sleeve shirts, pants, hats and sunglasses. • Children under 6 months: Ask a doctor.

Inactive Ingredients

Aqua (Water), C12-15 Alkyl Benzoate, Dibutyl Adipate, Butyloctyl Salicylate, Caprylic/Capric Triglyceride, Polyglyceryl-2 Dipolyhydroxystearate, Propanediol, Polyglyceryl-3 Diisostearate, Triethoxycaprylylsilane, 1,2-Hexanediol, C15-19 Alkane, Glycerin, Polyhydroxystearic Acid, Maris Sal (Sea Salt), Hydroxyacetophenone, Bisabolol, Stearalkonium Hectorite, Magnesium Sulfate, Allantoin, Hydrogenated Palm Oil, Tocopherol, Hydrogenated Rapeseed Oil, Glycine Soja (Soybean) Oil, Beta-Sitosterol, Ethylhexylglycerin, Propylene Carbonate, Squalene.

Questions or Comments?

info@annalotan.us
Tel.: (781) 281 0954

TENDER LOVING CARE
DERMATOLOGICALLY TESTED
FOR SENSITIVE SKIN

For All Skin Types

Experience superior sun protection with a silky-smooth touch. This fragrance- free lotion is powered exclusively by Zinc Oxide, providing a safe and effective mineral shield-free of chemical UV filters.

Unlike traditional mineral sunscreens, its creamy texture is effortlessly absorbed with several massage motions without leaving a heavy white cast on the skin making it perfect for daily wear-even under makeup.

Infused with a soothing blend of Bisabolol and Allantoin, plus potent antioxidants such as Vitamin E (Toco-pherol) and Hydroxyacetophenone, this formula helps prevent free radical damage essential during sun exposure.

Replenishing seed oils and phytosterols reinforce the skin‘s natural barrier, while Dead Sea minerals enhance long-lasting moisture retention. The unique water- in-oil emulsion resists wash-off, locking in softness and elasticity for all-day comfort.

How to Use: Apply generously to face and neck before sun exposure. Gently massage in any initial white tint, which disappears within seconds, leaving skin smooth and protected. Reapply as needed based on individual sun sensitivity.

Distributed by:
Catherine Hinds Institute
300 Wildwood Ave. Woburn,
MA 01801
Orders@catherinehinds.edu
Tel.: (781) 935-3344

Imported by: Anna Lotan USA Inc.
16 Wheeling Ave, Woburn, MA 01801